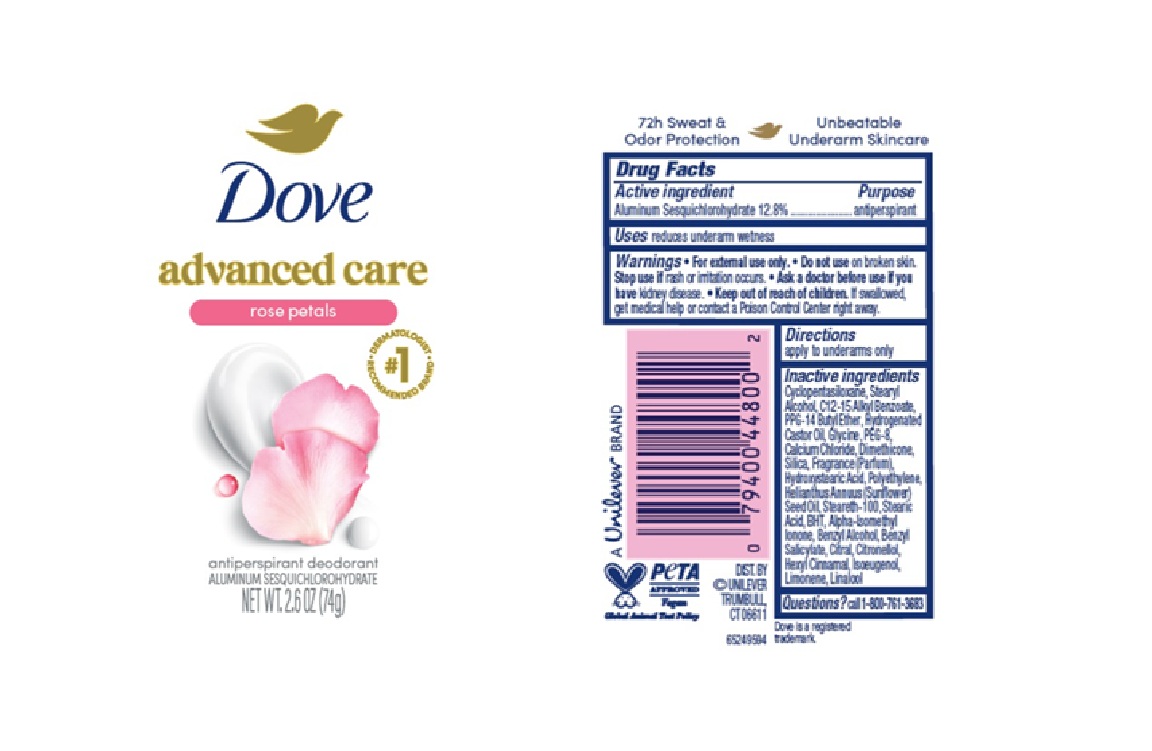 DRUG LABEL: Dove
NDC: 64942-2421 | Form: STICK
Manufacturer: Conopco d/b/a Unilever
Category: otc | Type: HUMAN OTC DRUG LABEL
Date: 20260105

ACTIVE INGREDIENTS: ALUMINUM SESQUICHLOROHYDRATE 12.8 g/100 g
INACTIVE INGREDIENTS: PPG-14 BUTYL ETHER; CALCIUM CHLORIDE; CITRONELLOL; HYDROGENATED CASTOR OIL; GLYCINE; CITRAL; ISOEUGENOL; DIMETHICONE; CYCLOPENTASILOXANE; STEARETH-100; STEARYL ALCOHOL; ALPHA-ISOMETHYL IONONE; BENZYL ALCOHOL; BENZYL SALICYLATE; LIMONENE, (+)-; STEARIC ACID; HEXYL CINNAMAL; LINALOOL; SILICA; HYDROXYSTEARIC ACID; POLYETHYLENE; HELIANTHUS ANNUUS (SUNFLOWER) SEED OIL; BHT; C12-15 ALKYL BENZOATE; PEG-8

Dove Advanced Care Rose Petals Antiperspirant Deodorant

DESCRIPTION

Dove Advanced Care Rose Petals Antiperspirant Deodorant

ACTIVE INGREDIENT

Aluminum Sesquichlorohydrate

PURPOSE

Antiperspirant

INDICATIONS AND USAGE

• reduces underarm wetness

WARNINGS

• For external use only.
• Do not use on broken skin. • Stop use if rash or irritation occurs.• Ask a doctor before use if you have kidney disease. If swallowed,get medical help or contact a Poison Control Center right away.

• KEEP OUT OF REACH OF CHILDREN.

DOSAGE AND ADMINISTRATION

apply to underarms only

INACTIVE INGREDIENT

Cyclopentasiloxane, StearylAlcohol, C12-15 Alkyl Benzoate, PPG-14 Butyl Ether, Hydrogenated Castor Oil, Glycine, PEG-8, Calcium Chloride, Dimethicone, Silica, Fragrance (Parfum), Hydroxystearic Acid, Polyethylene, Helianthus Annuus (Sunflower)
Seed Oil, Steareth-100, Stearic Acid, BHT, Alpha-Isomethyl Ionone, Benzyl Alcohol, Benzyl Salicylate, Citral, Citronellol, Hexyl Cinnamal, Isoeugenol, Limonene, Linalool

QUESTIONS

Call 1-800-761-3683